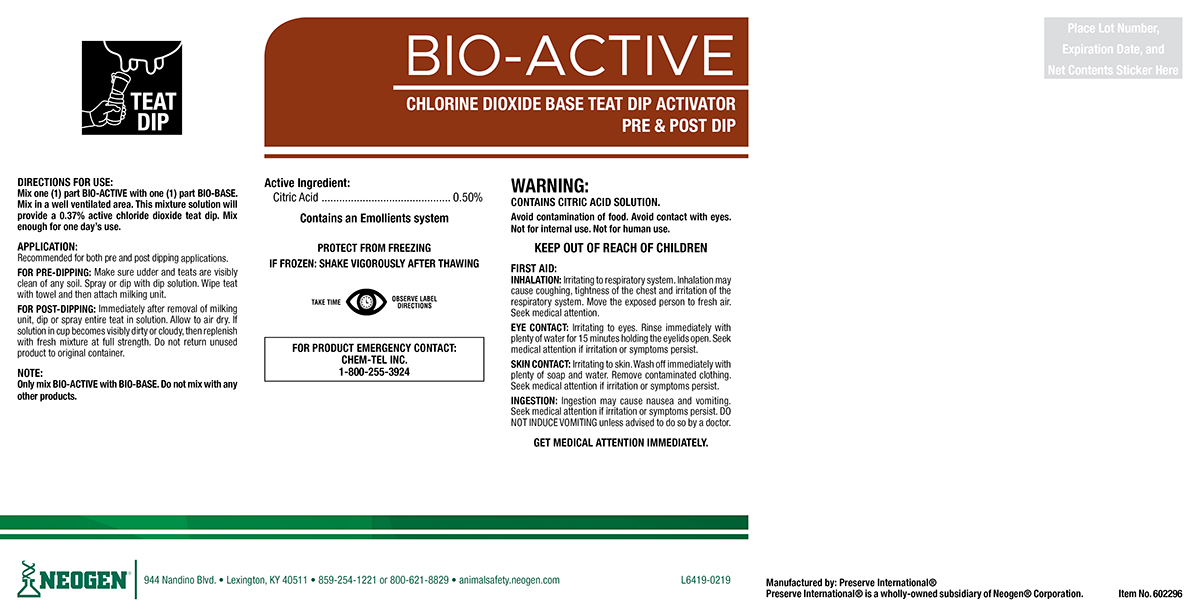 DRUG LABEL: Bio-Active
NDC: 60648-9012 | Form: SOLUTION
Manufacturer: Preserve International
Category: animal | Type: OTC ANIMAL DRUG LABEL
Date: 20190517

ACTIVE INGREDIENTS: ANHYDROUS CITRIC ACID 5.36 g/1 L

BIO-ACTIVE

DIRECTIONS FOR USE:

Mix one (1) part BIO-ACTIVE with one (1) part BIO-BASE. Mix in a well ventilated area. This mixture solution will provide a 0.37% active chlorine dioxide teat dip. Mix enough for one day's use.

APPLICATION:

Recommended for both pre and post dipping applications.

FOR PRE-DIPPING: Make sure udder and teats are visibly clean of any soil. Spray or dip with dip solution. Wipe teat with towel and then attach milking unit.

FOR POST-DIPPING: Immediately after removal of milking unit, dip or spray entire teat in solution. Allow to air dry. If solution in cup becomes visibly dirty or cloudy, then replenish with fresh mixture at full strength. Do not return unused product to original container.

NOTE:

Only mix BIO-ACTIVE with BIO-BASE. Do not mix with any other products.

WARNINGS AND PRECAUTIONS

PROTECT FROM FREEZING

IF FROZEN: SHAKE VIGOROUSLY AFTER THAWING

WARNINGS AND PRECAUTIONS

TAKE TIME OBSERVE LABEL DIRECTIONS

WARNING:

CONTAINS CITRIC ACID SOLUTION

Avoid contamination of food. Avoid contact with eyes. Not for internal use. Not for human use.

KEEP OUT OF REACH OF CHILDREN

FIRST AID:

INHALATION: Irritating to respiratory system. Inhalation may cause coughing, tightness of the chest and irritation of the respiratory system. Move the exposed person to fresh air. Seek medical attention.

EYE CONTACT: Irritating to eyes. Rinse immediately with plenty of water for 15 minutes holding the eyelids open. Seek medical attention if irritation or symptoms persist.

SKIN CONTACT: Irritating to skin. Wash off immediately with plenty of soap and water. Remove contamianted clothing. Seek medical attention if irritation or symptoms persist.

INGESTION: Ingestion may cause nausea and vomiting. Seek medical attention if irritation or symptoms persist. DO NOT INDUCE VOMITING unless advised to do so by a doctor.
GET MEDICAL ATTENTION IMMEDIATELY.

FOR PRODUCT EMERGENCY CONTACT: Chem-Tel Inc. 1-800-255-3924

PACKAGE LABEL

BIO-ACTIVE

CHLORINE DIOXIDE BASE TEAT DIP ACTIVATOR

PRE & POST DIP

Active Ingredients:

Citric Acid..........................0.50%
Contains an Emollients system

Manufactured By: Preserve International®

Preserve International® is a wholly-owned subsidiary of Neogen® Corporation.

NEOGEN®

944 Nandino Blvd.

Lexington, KY 40511

859-254-1221 or 800-621-8829

animalsafety.neogen.com